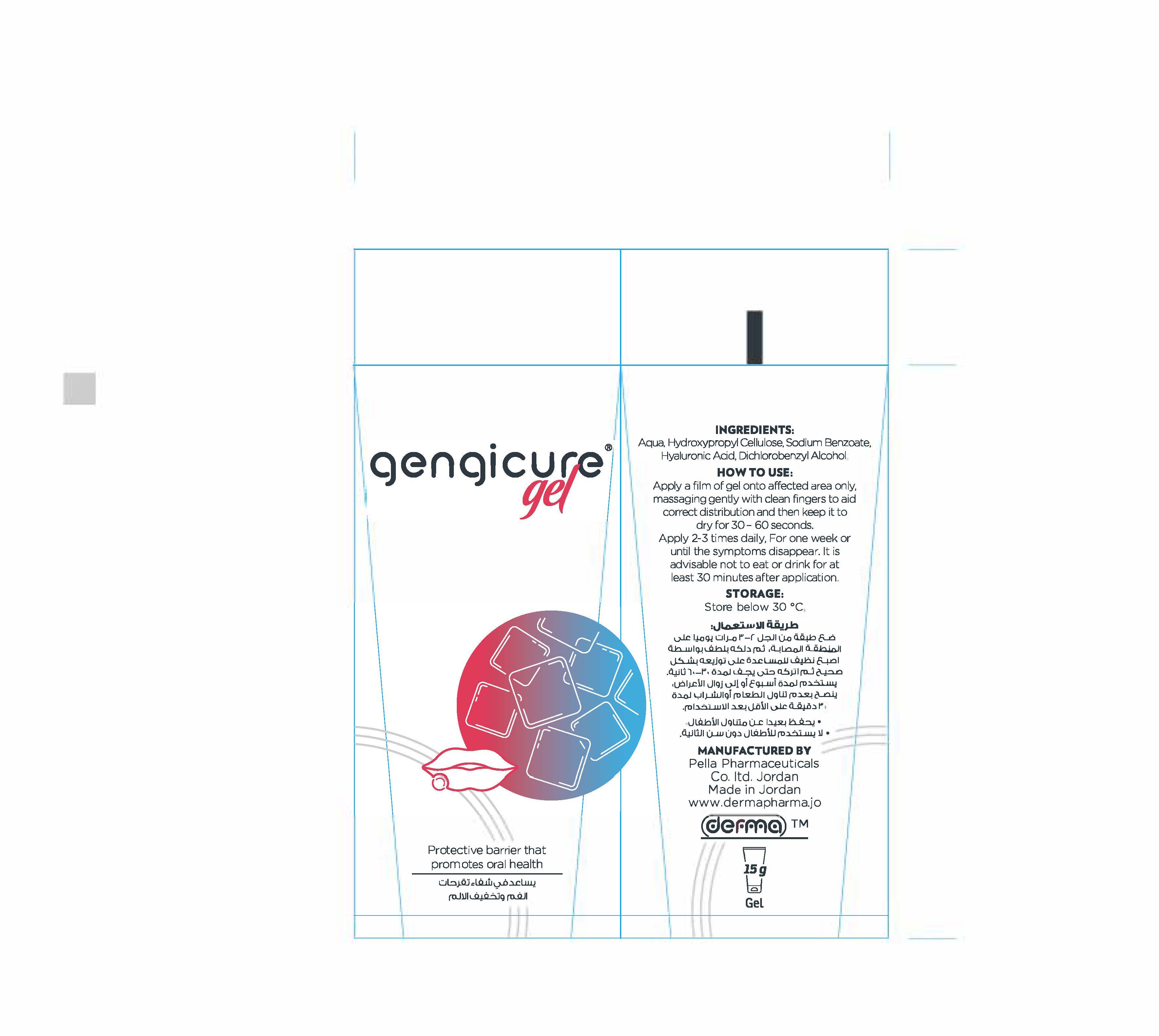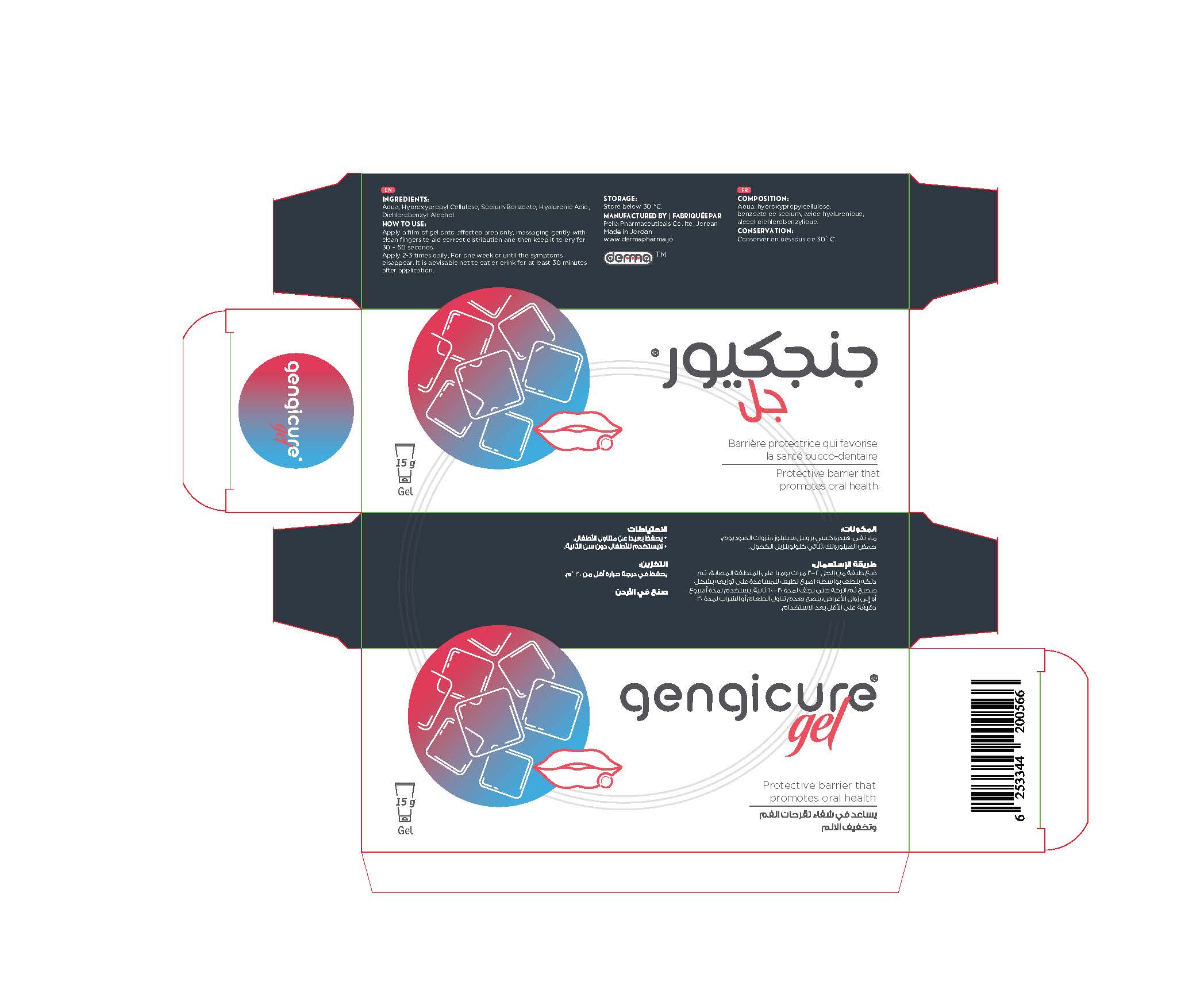 DRUG LABEL: Gengicure
NDC: 82160-566 | Form: GEL
Manufacturer: Pella Pharmaceuticals Co. Ltd
Category: otc | Type: HUMAN OTC DRUG LABEL
Date: 20211206

ACTIVE INGREDIENTS: HYALURONIC ACID 0.3 mg/15 g
INACTIVE INGREDIENTS: WATER; HYDROXYPROPYL CELLULOSE, UNSPECIFIED; DICHLOROBENZYL ALCOHOL; SODIUM BENZOATE

Gengicure

Forms and Presentation

Gel: Tube 15 g

Active Ingredient

Hyaluronic Acid

Inactive Ingredients

Aqua, Hydroxypropyl Cellulose, Sodium Benzoate and Dichlorobenzyl Alcohol.

Purpose

Helps healing internal and external mouth ulcers and relieving pain

Properties

gengicure® gel has a special formula immediately reduces pain and promotes the treatment of oral mucosal ulcers by accelerating normal healing process because it contains hyaluronic acid, a natural substance found in the connective tissues of the body. When applied to the ulcers it stimulates the production of new healthy tissue.
Paraben Free
Sugar Free
Colorants Free

Indication

gengicure ®gel helps healing internal and external mouth ulcers and relieving pain

Precautions

Keep out of reach of children

Warnings

- Do not swallow the product
- If symptoms persist consult your doctor

Contraindication

- Hypersensitivity to any of the components
- Do not use for children under 2 years

Pregnancy and Lactation

Ask your doctor or pharmacist for advice before using any product.
If you want to apply the gel during pregnancy or lactation then discuss this with your doctor

Interactions

No interactions between gengicure® gel and other drugs or substances are known or suspected.

Side effects

There are no known side effects

Dosage and administration

Apply a film of gel onto affected area only, massaging gently with clean fingers to aid its correct distribution and then keep it to dry for 30 – 60 seconds.
Apply 2-3 times daily, for one week or until the symptoms disappear.
It is advisable not to eat or drink for at least 30 minutes after application.

Storage Conditions

Store below 30◦C.